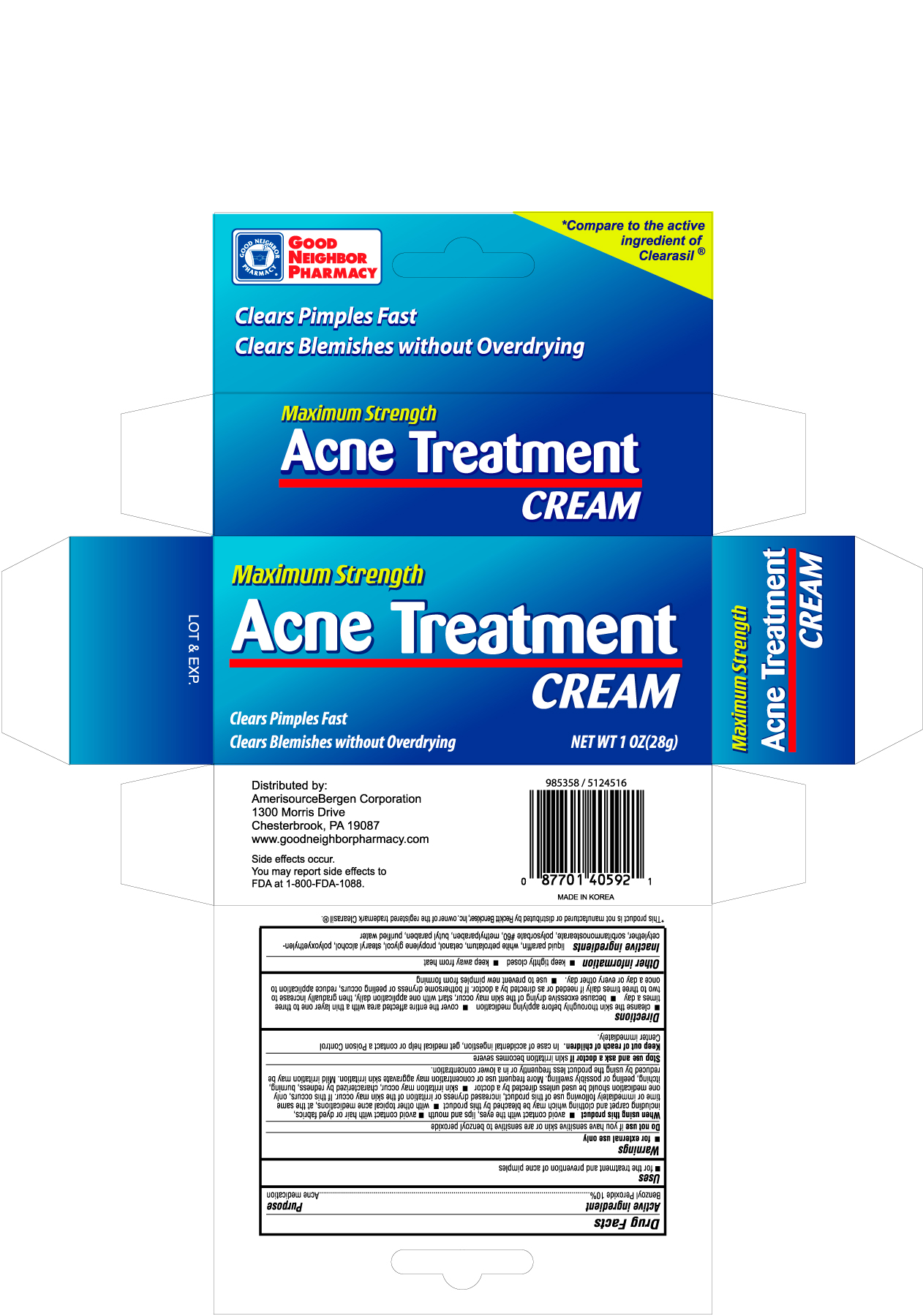 DRUG LABEL: GOOD NEIGHBOR PHARMACY ACNE TREATMENT
NDC: 68169-4059 | Form: CREAM
Manufacturer: TAI GUK PHARM. CO., LTD.
Category: otc | Type: HUMAN OTC DRUG LABEL
Date: 20101117

ACTIVE INGREDIENTS: BENZOYL PEROXIDE 10 g/100 g
INACTIVE INGREDIENTS: MINERAL OIL; PETROLATUM; PROPYLENE GLYCOL; STEARYL ALCOHOL; POLYSORBATE 60; METHYLPARABEN; WATER

Drug Facts

Active ingredient Purpose

Benzoyl Peroxide 10% ....................................................Acne medication

Uses

- for the treatment and prevention of acne pimples

Warnings

- for external use only

Do not use if you have sensitive skin or are sensitive to benzoyl peroxide

When using this product

- avoid contact with the eyes, lips and mouth
- avoid contact with hair or dyed fabrics, including carpet and clothing which may be bleached by this product
- with other topical acne medications, at the same time or immediately following use of this product, increased dryness or irritation of the skin may occur. If this occurs, only one medication should be used unless directed by a doctor
- skin irritation may occur, characterized by redness, burning, itching, peeling or possibly swelling. More frequent use or concentration may aggravate skin irritation. Mild irritation may be reduced by using the product less frequently or in a lower concentration

Stop use and ask a doctor if skin irritation becomes severe

Keep out of reach of children. In case of accidental ingestion, get medical help or contact a Poison Control Center immediately.

Directions

- cleanse the skin thoroughly before applying medication
- cover the entire affected area with a thin layer one to three times a day
- because excessive drying of the skin may occur, start with one application daily, then gradually increase to two to three times daily if needed or as directed by a doctor. If bothersome dryness or peeling occurs, reduce application to once a day or every other day
- use to prevent new pimples from forming

Other information

- keep tightly closed
- keep away from heat

Inactive ingredients

liquid paraffin, white petrolatum, cetanol, propylene glycol, stearyl alcohol, polyoxyethylancetylether, sorbitanmonostearate, polysorbate #60, methylparaben, butyl paraben, purified water

DOSAGE AND ADMINISTRATION

Distributed by:

Amerisource Bergen Corporation

1300 Morris Drive

Chesterbrook, PA 19087

www.goodneighborpharmacy.com

PACKAGE LABEL

Enter section text here